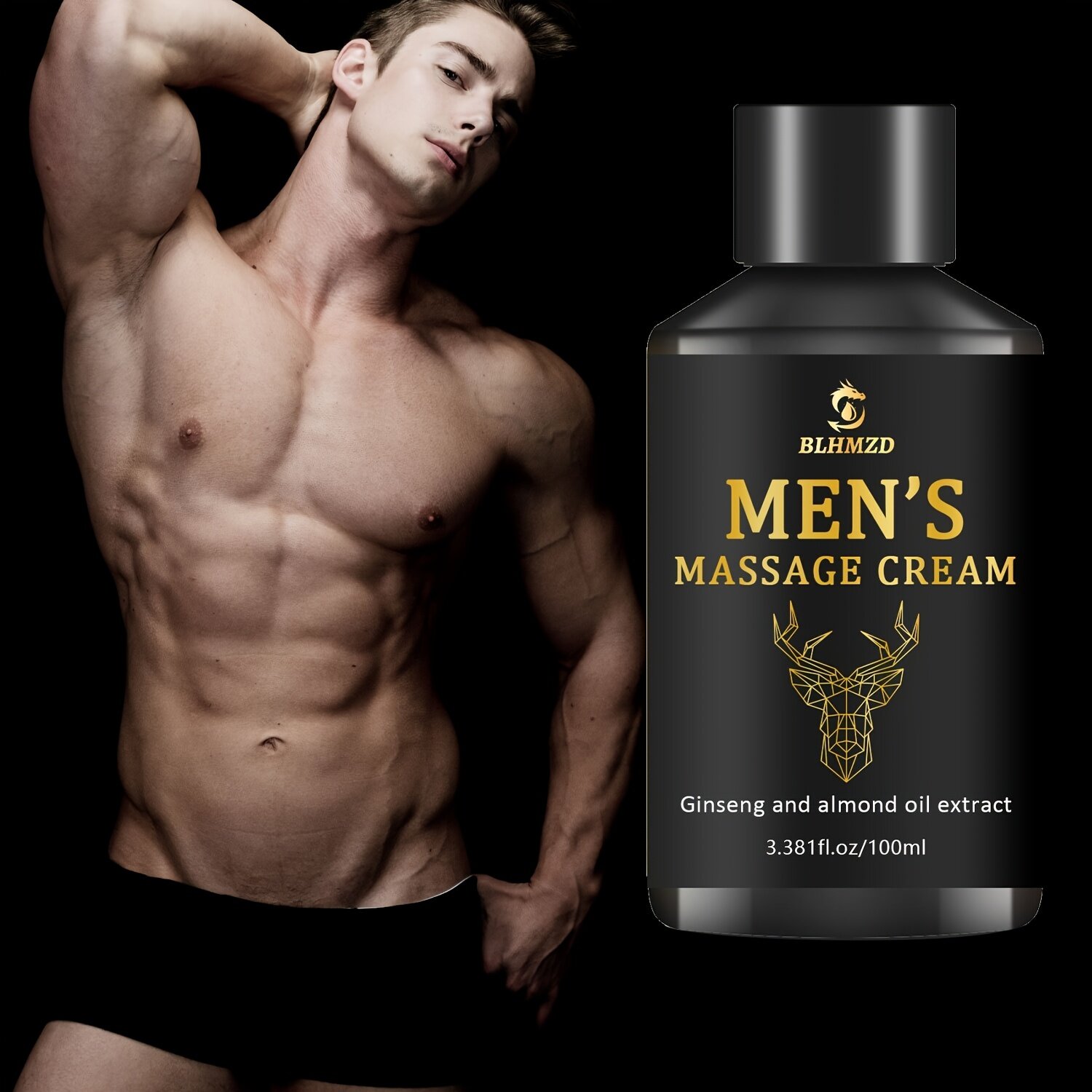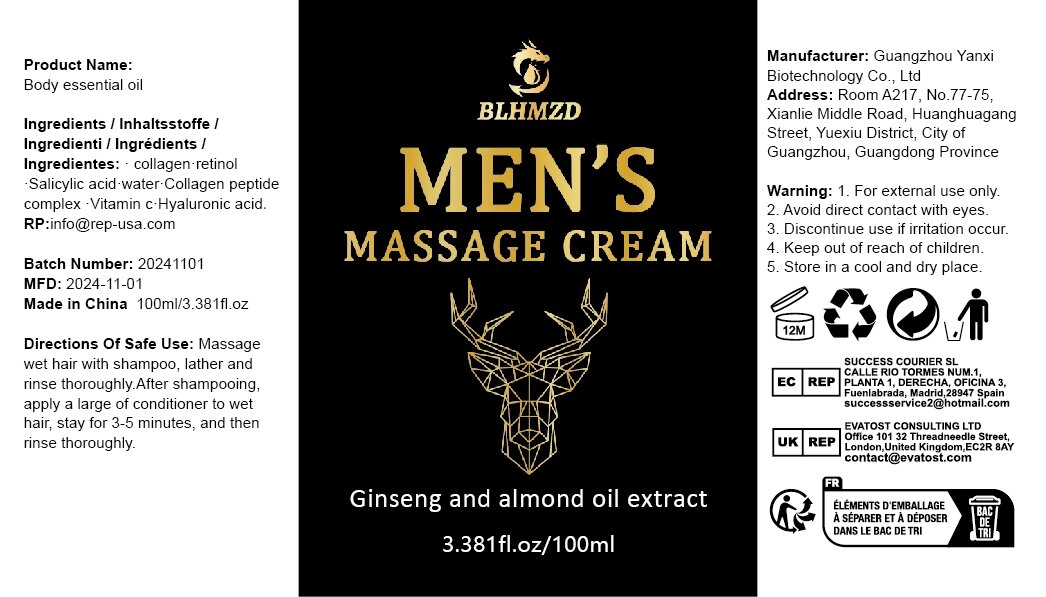 DRUG LABEL: Body essential oil
NDC: 84025-316 | Form: OIL
Manufacturer: Guangzhou Yanxi Biotechnology Co., Ltd
Category: otc | Type: HUMAN OTC DRUG LABEL
Date: 20250107

ACTIVE INGREDIENTS: HYALURONIC ACID 3 mg/100 mL; RETINOL 5 mg/100 mL
INACTIVE INGREDIENTS: WATER

DOSAGE AND ADMINISTRATION

Massage wet hair with shampoo, lather andrinse thoroughly. After shampooing.apply a large of conditioner to wethair, stay for 3-5 minutes, and thenrinse thoroughly.

WARNINGS

Keep out of children

INACTIVE INGREDIENT

Aqua

INDICATIONS AND USAGE

for daily body care

keep out of children

PURPOSE

Moisturize and hydrate the skin